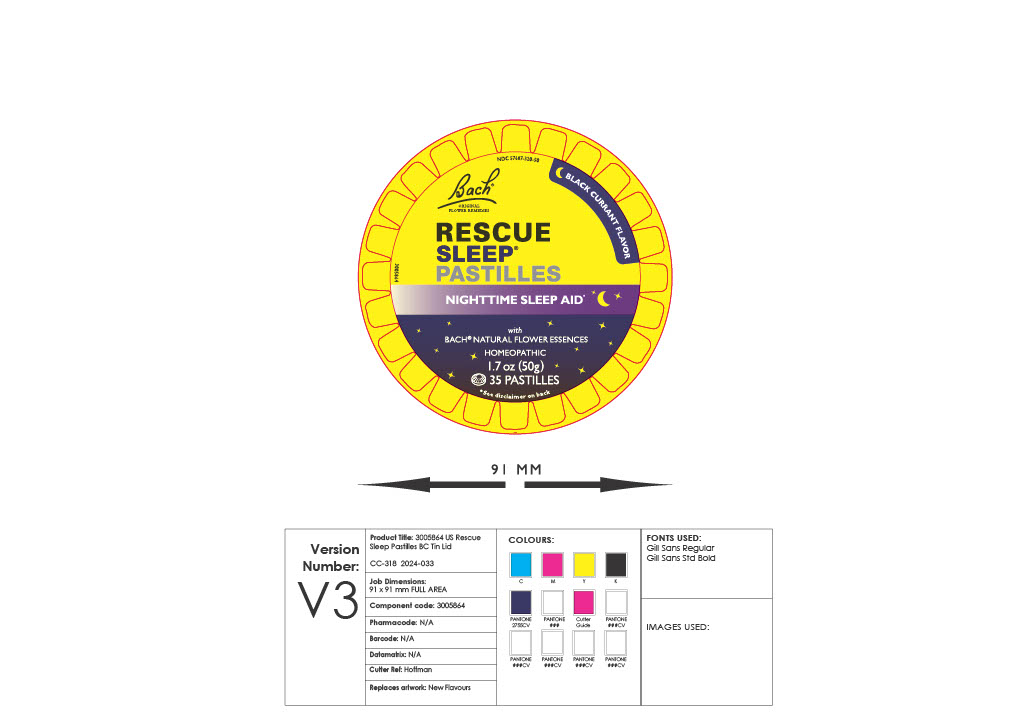 DRUG LABEL: Rescue Sleep Pastilles Blackcurrant
NDC: 57687-320 | Form: LOZENGE
Manufacturer: Nelson Bach USA Ltd
Category: homeopathic | Type: HUMAN OTC DRUG LABEL
Date: 20240624

ACTIVE INGREDIENTS: HELIANTHEMUM NUMMULARIUM FLOWER 5 [hp_X]/1 1; IMPATIENS GLANDULIFERA FLOWER 5 [hp_X]/1 1; AESCULUS HIPPOCASTANUM FLOWER 5 [hp_X]/1 1; CLEMATIS VITALBA PRE-FLOWERING TOP 5 [hp_X]/1 1; PRUNUS CERASIFERA FLOWER 5 [hp_X]/1 1; ORNITHOGALUM UMBELLATUM 5 [hp_X]/1 1
INACTIVE INGREDIENTS: SORBITOL; XYLITOL; CABBAGE; CITRIC ACID MONOHYDRATE; ISOMALT; ACACIA; BLACK CARROT; YELLOW WAX; PALM OIL; EUROPEAN ELDERBERRY JUICE; BLACK CURRANT; MALTITOL

Rescue Sleep Pastilles Blackcurrant

ACTIVE INGREDIENT

Active ingredients (each 5X HPUS): Cherry Plum, Clematis, Impatiens, Rock Rose, Star of Bethlehem, White Chestnut. ‘HPUS’ indicates ingredients are in the official Homeopathic Pharmacopoeia of the United States.

INDICATIONS AND USAGE

Purpose/Use: For relief of occasional sleeplessness caused by stress & repetitive thoughts

WARNINGS

Warnings: Stop using & ask a doctor if sleeplessness persists for more than 2 weeks: insomnia can be a symptom of a serious underlying medical illness. Excessive consumption may induce a mild laxative effect. If pregnant or breastfeeding, ask a doctor before use. Keep out of reach of children. Product can pose a choking hazard.

DOSAGE AND ADMINISTRATION

Directions: Adults & children aged 6 & older, consume 1 pastille & completely dissolve before sleep. Do not go to sleep with undissolved pastille in mouth

Other information: Do not use if tamper-evident seal is missing or broken.

FOR HUMAN CONSUMPTION ONLY, NOT FOR ANIMAL USE.

STORAGE AND HANDLING

Store below 77°F

INACTIVE INGREDIENT

Inactive ingredients: beeswax, black carrot extract, black currant (as flavor), citric acid, elder extract, gum arabic, isomalt, maltitol, red cabbage extract, sorbitol, sustainable palm kernel oil, xylitol.

QUESTIONS

RESCUE SLEEP® is a homeopathic dilution: see NelsonsDilution.com for details. Trademarks on pack are owned by the Nelsons’ Group. Questions: (800) 319-9151. Nelsons.com. Dist by: Nelson Bach USA Ltd, N. Andover, MA 01845. Made in Switzerland. Made in an FDA registered pharmaceutical facility. aims based on traditional homeopathic practice, not accepted medical evidence. Not FDA evaluated.

Keep out of reach of children. Product can pose a choking hazard

PURPOSE

Active ingredients (each 5X HPUS): Cherry Plum, Clematis, Impatiens, Rock Rose, Star of Bethlehem, White Chestnut. ‘HPUS’ indicates ingredients are in the official Homeopathic Pharmacopoeia of the United States.

PACKAGE LABEL

NDC 57687-320-50

Bach Original Flower Essences

Rescue Sleep Pastilles - Blackcurrant flavour

Nighttime sleep aid

with natural bach flower essences

Homeopathic

1.7 oz (50g)

35 pastilles

see disclaimer on back panel